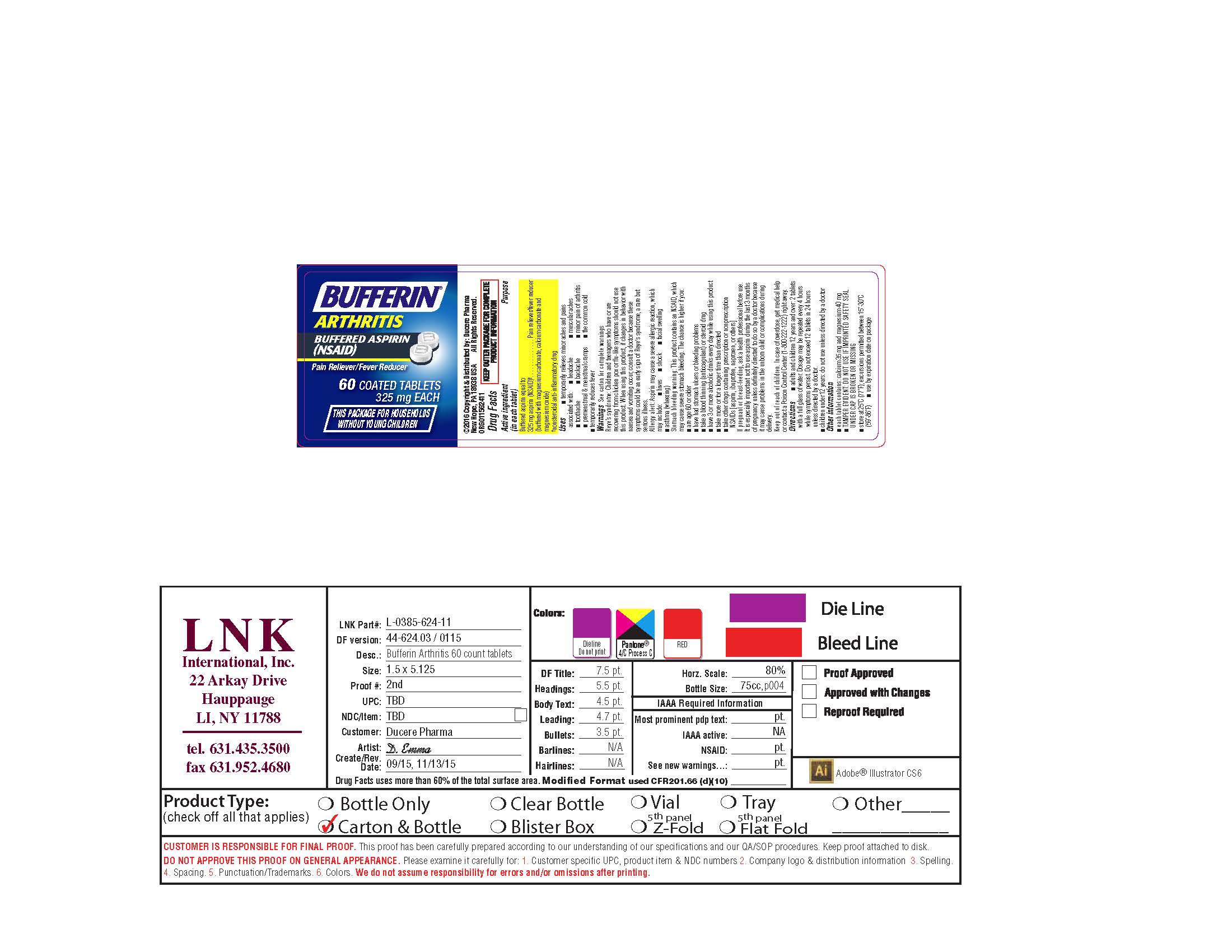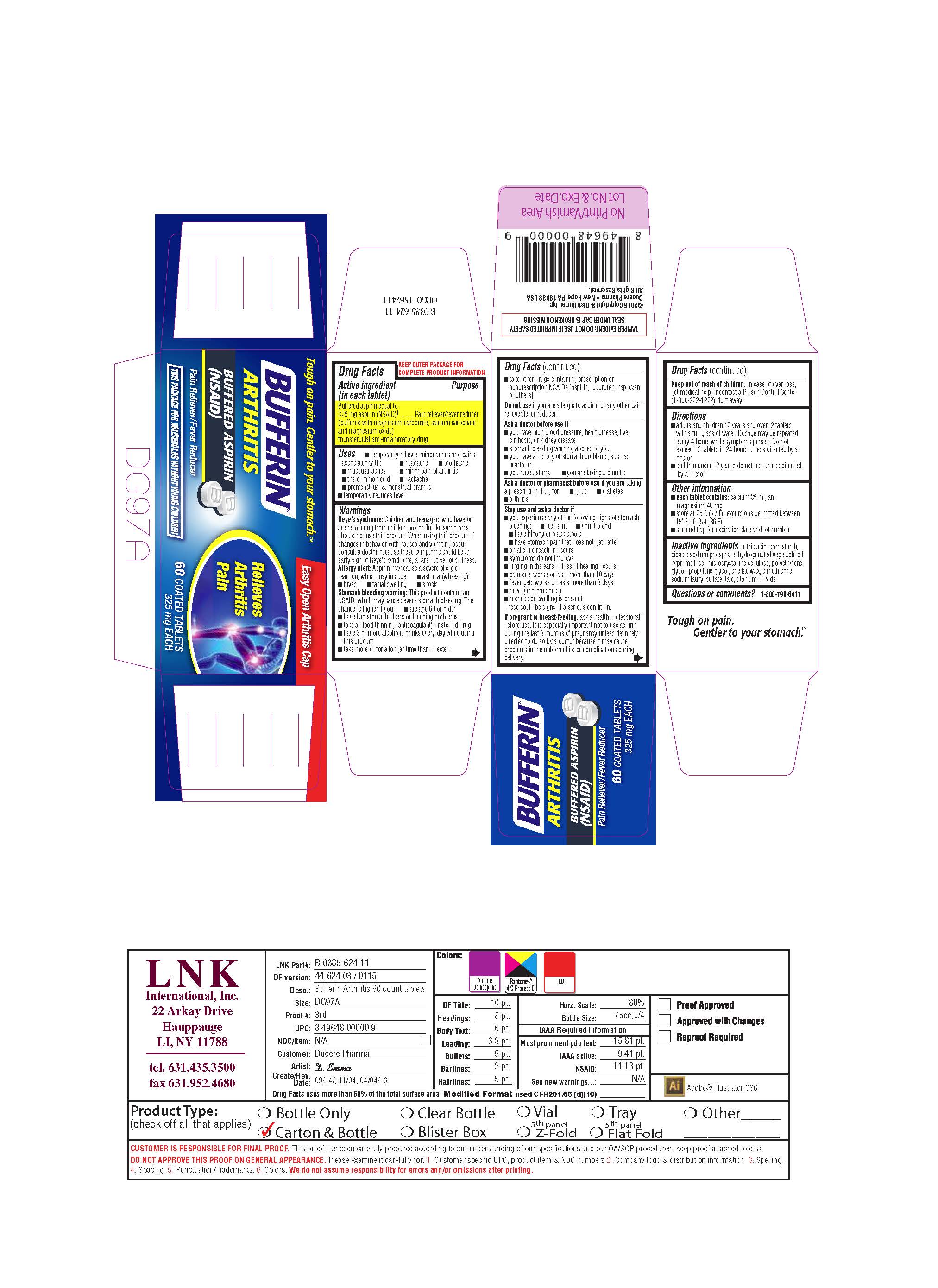 DRUG LABEL: Bufferin Arthritis
NDC: 55741-000 | Form: TABLET
Manufacturer: Dr. Reddy's Laboratories Inc.
Category: otc | Type: HUMAN OTC DRUG LABEL
Date: 20191209

ACTIVE INGREDIENTS: Aspirin 325 mg/1 1
INACTIVE INGREDIENTS: citric acid monohydrate; starch, corn; Sodium Phosphate, Dibasic; hypromelloses; cellulose, microcrystalline; Polyethylene Glycol, Unspecified; propylene glycol; sodium lauryl sulfate; talc; titanium dioxide

Bufferin Arthritis

Drug Facts

Active ingredient (in each tablet)

Buffered aspirin equal to 325 mg aspirin (NSAID) [nonsteroidal anti-inflammatory drug] (buffered with magnesium carbonate, calcium carbonate and magnesium oxide)

Purpose

Pain reliever/fever reducer

Uses

- temporarily relieves minor aches and pains associated with:
  - headache
  - minor pain of arthritis
  - backache
  - toothache
  - the common cold
  - muscular aches
  - premenstrual & menstrual cramps
- temporarily reduces fever

Warnings

Reye's syndrome

DO NOT USE

Children and teenagers who have or are recovering from chicken pox or flu-like symptoms should not use this product.

When using this product, if changes in behavior with nausea and vomiting occur, consult a doctor because these symptoms could be an early sign of Reye's syndrome, a rare but serious illness.

Allergy alert

Aspirin may cause a severe allergic reaction, which may include:

- hives
- facial swelling
- shock
- asthma (wheezing)

Stomach bleeding warning

This product contains an NSAID, which may cause severe stomach bleeding. The chance is higher if you:

- are age 60 or older
- have had stomach ulcers or bleeding problems
- take a blood thinning (anticoagulant) or steroid drug
- take other drugs containing prescription or nonprescription NSAIDs [aspirin, ibuprofen, naproxen, or others]
- have 3 or more alcoholic drinks every day while using this product
- take more or for a longer time than directed
- take other drugs containing prescription or nonprescription NSAIDs [aspirin, ibuprofen, naproxen, or others]

Do not use if you are allergic to aspirin or any other pain reliever/fever reducer.

Ask a doctor before use if

- you have high blood pressure, heart disease, liver cirrhosis, or kidney disease
- stomach bleeding warning applies to you
- you have a history of stomach problems, such as heartburn
- you have asthma
- you are taking a diuretic

Ask a doctor or pharmacist before use if you are taking a prescription drug for

- gout
- diabetes
- arthritis

Stop use and ask a doctor if

- you experience any of the following signs of stomach bleeding:
  - feel faint
  - vomit blood
  - have bloody or black stools
  - have stomach pain that does not get better
- an allergic reaction occurs
- symptoms do not improve
- ringing in the ears or loss of hearing occurs
- pain gets worse or lasts more than 10 days
- fever gets worse or lasts more than 3 days
- new symptoms occur
- redness or swelling is present

These could be signs of a serious condition.

PREGNANCY OR BREAST FEEDING

If pregnant or breast-feeding, ask a health professional before use. It is especially important not to use aspirin during the last 3 months of pregnancy unless definitely directed to do so by a doctor because it may cause problems in the unborn child or complications during delivery.

Keep out of reach of children. In case of overdose, get medical help or contact a Poison Control Center (1-800-222-1222) right away.

Directions

- adults and children 12 years and over: 2 tablets with a full glass of water. Dosage may be repeated every 4 hours while symptoms persist. Do not exceed 12 tablets in 24 hours unless directed by a doctor.
- children under 12 years: do not use unless directed by a doctor

Other information

- each tablet contains: calcium 35 mg and magnesium 40 mg
- store at 25°C (77°F); excursions permitted between 15°-30°C (59°-86°F)
- see end flap for expiration date and lot number

Inactive ingredients

citric acid, corn starch, dibasic sodium phosphate, hydrogenated vegetable oil, hypromellose, microcrystalline cellulose, polyethylene glycol, propylene glycol, shellac wax, simethicone, sodium lauryl sulfate, talc, titanium dioxide

Questions or comments?

1-800-790-6417

PRINCIPAL DISPLAY PANEL - 60 Tablet Bottle Box

Tough on pain. Gentler to your stomach.

BUFFERIN® Arthritis

BUFFERED ASPIRIN (NSAID)

Pain Reliever/Fever Reducer

60 COATED TABLETS
325 mg EACH

THIS PACKAGE FOR HOUSEHOLDS WITHOUT YOUNG CHILDREN